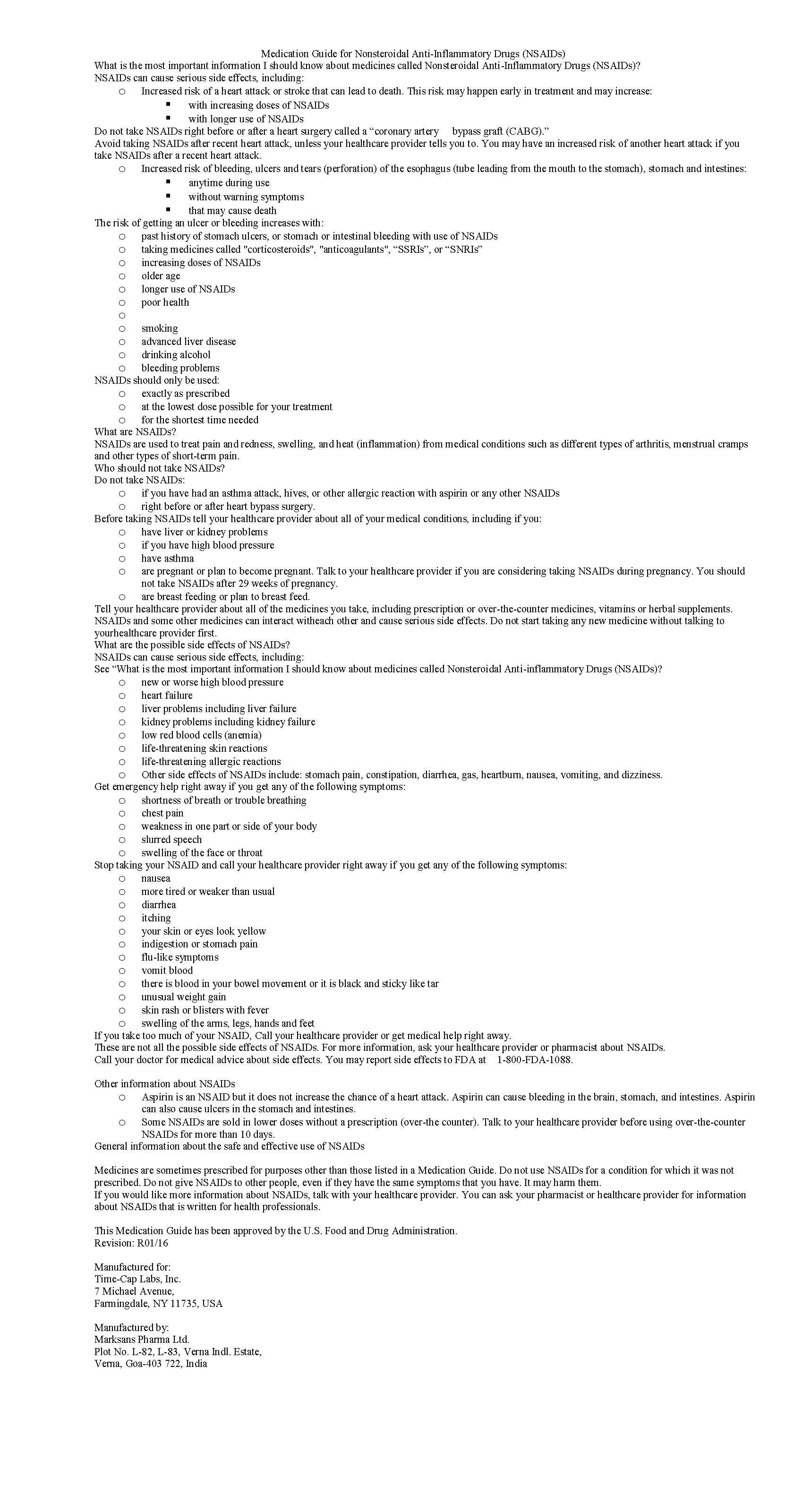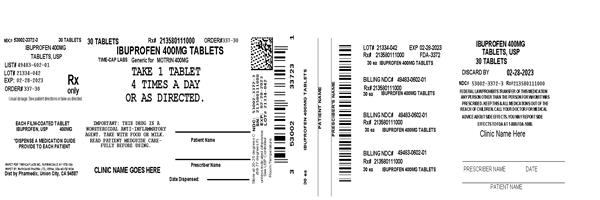 DRUG LABEL: IBUPROFEN
NDC: 53002-3372 | Form: TABLET, FILM COATED
Manufacturer: RPK Pharmaceuticals, Inc.
Category: prescription | Type: HUMAN PRESCRIPTION DRUG LABEL
Date: 20220330

ACTIVE INGREDIENTS: IBUPROFEN 400 mg/1 1
INACTIVE INGREDIENTS: SILICON DIOXIDE; CROSCARMELLOSE SODIUM; MAGNESIUM STEARATE; MICROCRYSTALLINE CELLULOSE; POLYETHYLENE GLYCOL, UNSPECIFIED; POLYVINYL ALCOHOL, UNSPECIFIED; STARCH, CORN; TALC; TITANIUM DIOXIDE

IBUPROFEN 400 MG - 600 MG AND 800 MG TABLETS

HOW SUPPLIED

Product: 53002-3372

NDC: 53002-3372-1 15 TABLET, FILM COATED in a BOTTLE

NDC: 53002-3372-3 30 TABLET, FILM COATED in a BOTTLE

NDC: 53002-3372-5 50 TABLET, FILM COATED in a BOTTLE